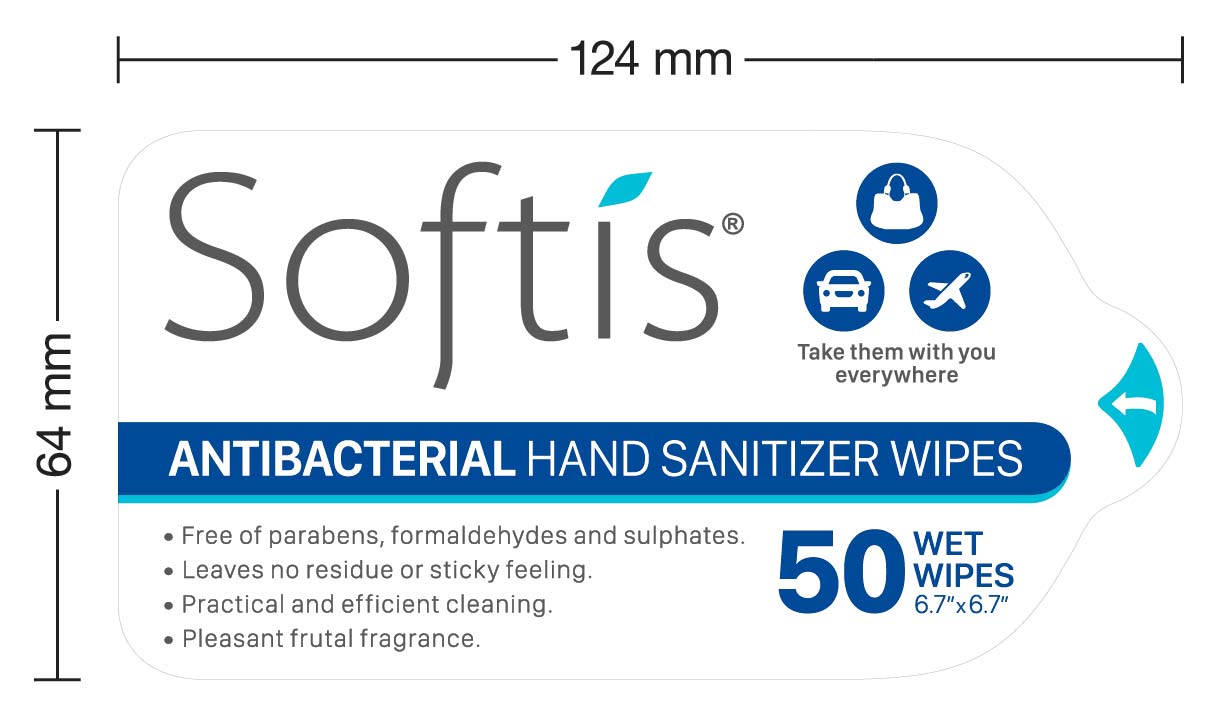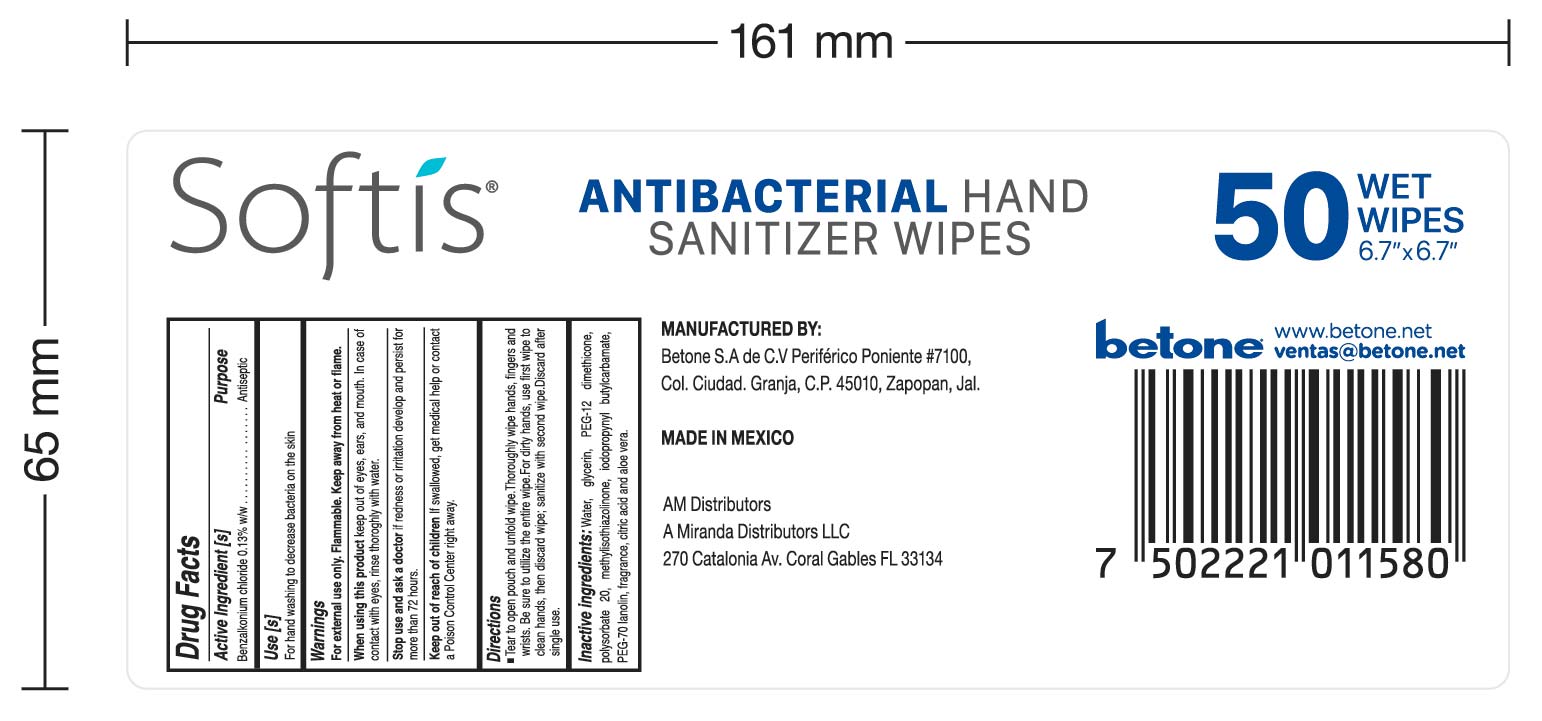 DRUG LABEL: SOFTIS
NDC: 77824-006 | Form: CLOTH
Manufacturer: Betone, S.A de C.V.
Category: otc | Type: HUMAN OTC DRUG LABEL
Date: 20201118

ACTIVE INGREDIENTS: BENZALKONIUM CHLORIDE 0.13 g/100 mL
INACTIVE INGREDIENTS: CITRIC ACID MONOHYDRATE 0.03 mL/100 mL; METHYLISOTHIAZOLINONE 0.13 mL/100 mL; ABRONIA FRAGRANS FLOWER 0.1 mL/100 mL; DIMETHICONE PEG-7 PANTHENYL PHOSPHATE (12 PANTHENOL) 0.2 mL/100 mL; GLYCERIN 1 mL/100 mL; ALOE VERA FLOWER 0.0004 mL/100 mL; WATER; IODOPROPYNYL BUTYLCARBAMATE 0.13 mL/100 mL; POLYSORBATE 20 0.15 mL/100 mL; PEG-70 LANOLIN 0.1 mL/100 mL

Antibacterial hand sanitizer wipes- BETONE (50 wipes)

Active Ingredient(s)

Benzalkonium chloride 0.13% w/w. Purpose: Antiseptic

Purpose

Antiseptic, Hand Sanitizer

Use

Hand Sanitizer to help reduce bacteria that potentially can cause disease. For use when soap and water are not available.

Warnings

For external use only. Flammable. Keep away from heat or flame

Do not use

- in children less than 2 months of age
- on open skin wounds

When using this product keep out of eyes, ears, and mouth. In case of contact with eyes, rinse eyes thoroughly with water.
Stop use and ask a doctor if irritation or rash occurs. These may be signs of a serious condition.
Keep out of reach of children. If swallowed, get medical help or contact a Poison Control Center right away.

Stop use and ask a doctor if irritation or rash occurs. These may be signs of a serious condition.

Keep out of reach of children. If swallowed, get medical help or contact a Poison Control Center right away.

Directions

- Place enough product on hands to cover all surfaces. Rub hands together until dry.
- Supervise children under 6 years of age when using this product to avoid swallowing.

Other information

- Store between 15-30C (59-86F)
- Avoid freezing and excessive heat above 40C (104F)

Inactive ingredients

Water, glycerin, DPEG-12 imethicone, Polysobarte 20, Methylisothiazolinone, iodopropinyl butylcarbameto, PEG-70 Lanolin, fragrance, citric acid and aloe vera.

Package Label - Principal Display Panel

250 g PDP NDC:77824-006-01